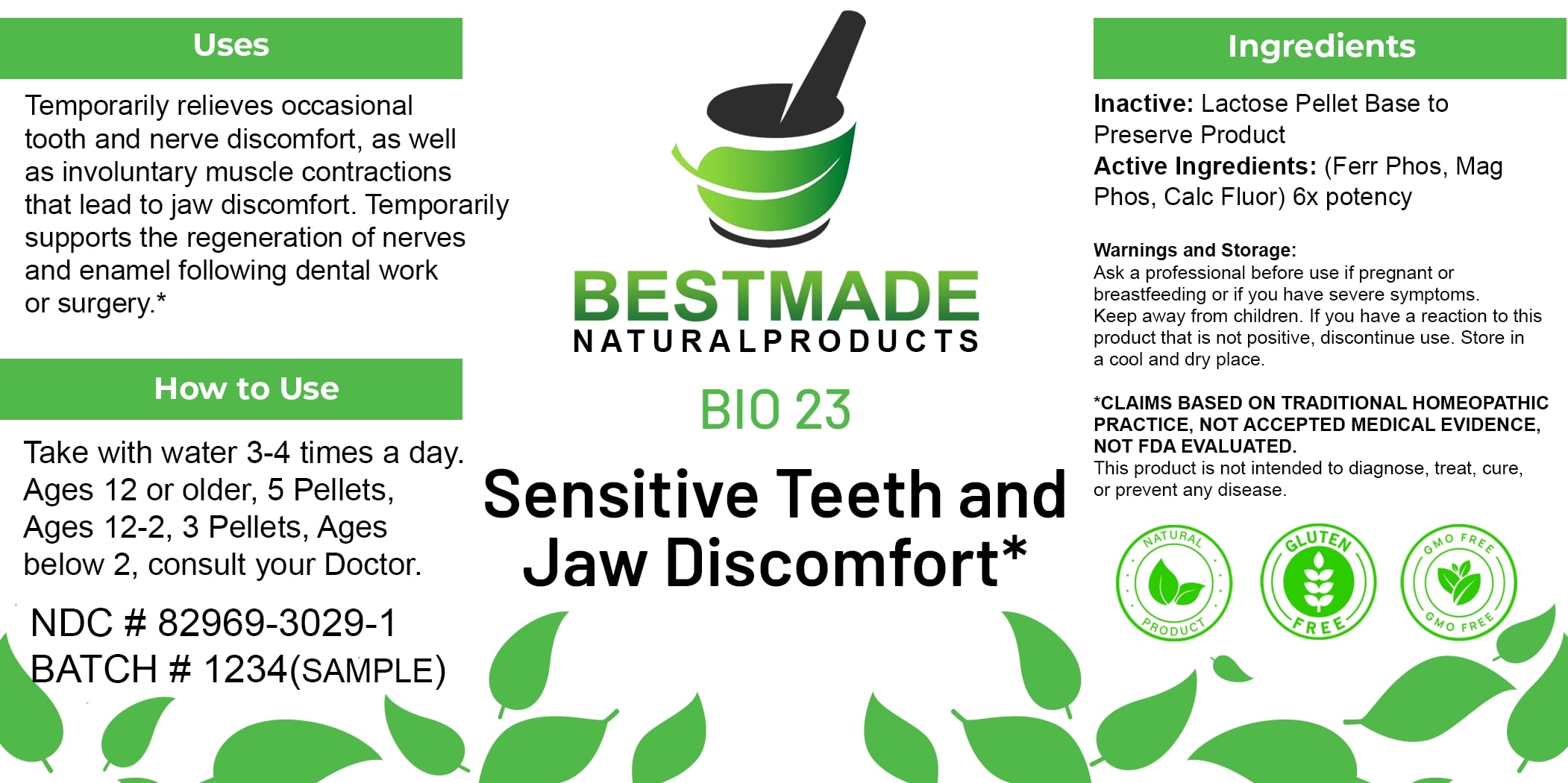 DRUG LABEL: Bestmade Natural Products Bio23
NDC: 82969-3023 | Form: TABLET, SOLUBLE
Manufacturer: Bestmade Natural Products
Category: homeopathic | Type: HUMAN OTC DRUG LABEL
Date: 20250323

ACTIVE INGREDIENTS: MAGNESIUM PHOSPHATE, DIBASIC TRIHYDRATE 6 [hp_X]/6 [hp_X]; CALCIUM FLUORIDE 6 [hp_X]/6 [hp_X]; FERRIC PYROPHOSPHATE 6 [hp_X]/6 [hp_X]
INACTIVE INGREDIENTS: LACTOSE, UNSPECIFIED FORM 6 [hp_X]/6 [hp_X]

bio23

DOSAGE AND ADMINISTRATION

How to Use

Take with water 3-4 times a day. Ages 12 or older, 5 Pellets, Ages 12-2, 3 Pellets, Ages below 2, consult your Doctor.

INACTIVE INGREDIENT

Ingredients

Inactive: Lactose Pellet Base to Preserve Product

ACTIVE INGREDIENT

Active Ingredients: (Ferr Phos, Mag Phos, Calc Fluor) 6x potency

Uses

Temporarily relieves occasional tooth and nerve discomfort, as well as involuntary muscle contractions that lead to jaw discomfort. Temporarily supports the regeneration of nerves and enamel following dental work or surgery.*

*CLAIMS BASED ON TRADITIONAL HOMEOPATHIC PRACTICE, NOT ACCEPTED MEDICAL EVIDENCE. NOT FDA EVALUATED.

This product is not intended to diagnose, treat, cure, or prevent any disease.

Uses

Temporarily relieves occasional tooth and nerve discomfort, as well as involuntary muscle contractions that lead to jaw discomfort. Temporarily supports the regeneration of nerves and enamel following dental work or surgery.*

*CLAIMS BASED ON TRADITIONAL HOMEOPATHIC PRACTICE, NOT ACCEPTED MEDICAL EVIDENCE. NOT FDA EVALUATED.

This product is not intended to diagnose, treat, cure, or prevent any disease.

KEEP OUT OF REACH OF CHILDREN

Warnings and Storage:

Ask a professional before use if pregnant or breastfeeding or if you have severe symptoms. Keep away from children. If you have a reaction to this product that is not positive, discontinue use. Store in a cool and dry place.

Warnings and Storage:

Ask a professional before use if pregnant or breastfeeding or if you have severe symptoms. Keep away from children. If you have a reaction to this product that is not positive, discontinue use. Store in a cool and dry place.

*CLAIMS BASED ON TRADITIONAL HOMEOPATHIC PRACTICE, NOT ACCEPTED MEDICAL EVIDENCE. NOT FDA EVALUATED.

This product is not intended to diagnose, treat, cure, or prevent any disease.

Entire package label